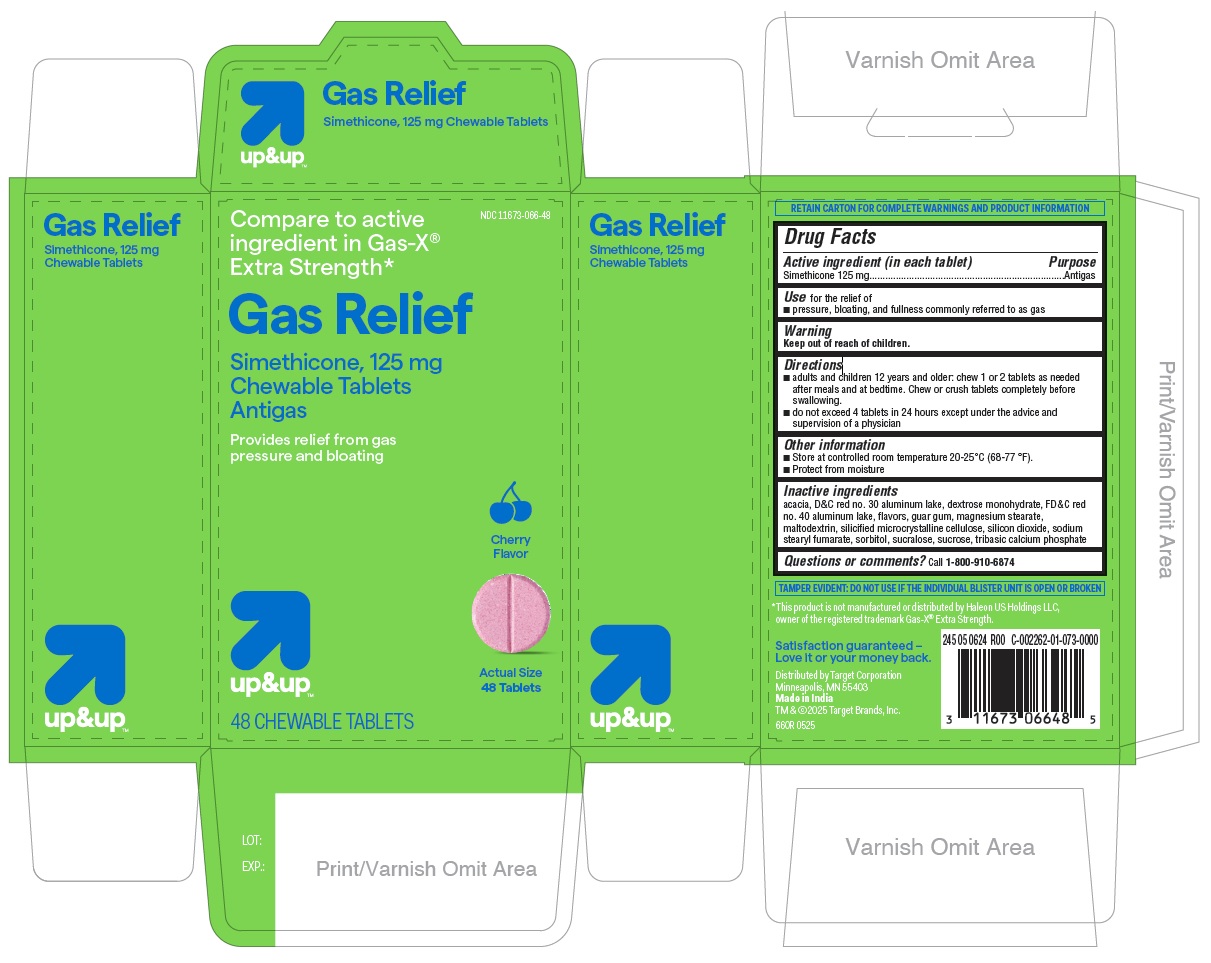 DRUG LABEL: Gas Relief - Cherry Flavor
NDC: 11673-066 | Form: TABLET, CHEWABLE
Manufacturer: TARGET CORPORATION
Category: otc | Type: HUMAN OTC DRUG LABEL
Date: 20250411

ACTIVE INGREDIENTS: DIMETHICONE 125 mg/1 1
INACTIVE INGREDIENTS: GUAR GUM; SILICON DIOXIDE; ACACIA; SORBITOL; SILICIFIED MICROCRYSTALLINE CELLULOSE (65 ?M); SODIUM STEARYL FUMARATE; D&C RED NO. 30 ALUMINUM LAKE; DEXTROSE MONOHYDRATE; TRIBASIC CALCIUM PHOSPHATE; FD&C RED NO. 40 ALUMINUM LAKE; SUCRALOSE; SUCROSE; MAGNESIUM STEARATE; MALTODEXTRIN

660R - Target Simethicone 125 mg Chewable tablets - Cherry Flavor

Drug Facts

Active ingredient (in each tablet)

Simethicone 125 mg

Purpose

Antigas

INDICATIONS AND USAGE

Use for the relief of

- pressure, bloating, and fullness commonly referred to as gas

Warning

Keep out of reach of children.

Directions

- adults and children 12 years and older: chew 1 or 2 tablets as needed after meals and at bedtime. Chew or crush tablets completely before swallowing.
- do not exceed 4 tablets in 24 hours except under the advice and supervision of a physician

Other information

- Store at controlled room temperature 20-25°C (68-77 °F).
- Protect from moisture

Inactive ingredients

acacia, D&C red no. 30 aluminum lake, dextrose monohydrate, FD&C red no. 40 aluminum lake, flavors, guar gum, magnesium stearate, maltodextrin, silicified microcrystalline cellulose, silicon dioxide, sodium stearyl fumarate, sorbitol, sucralose, sucrose, tribasic calcium phosphate

Questions or comments? Call 1-800-910-6874